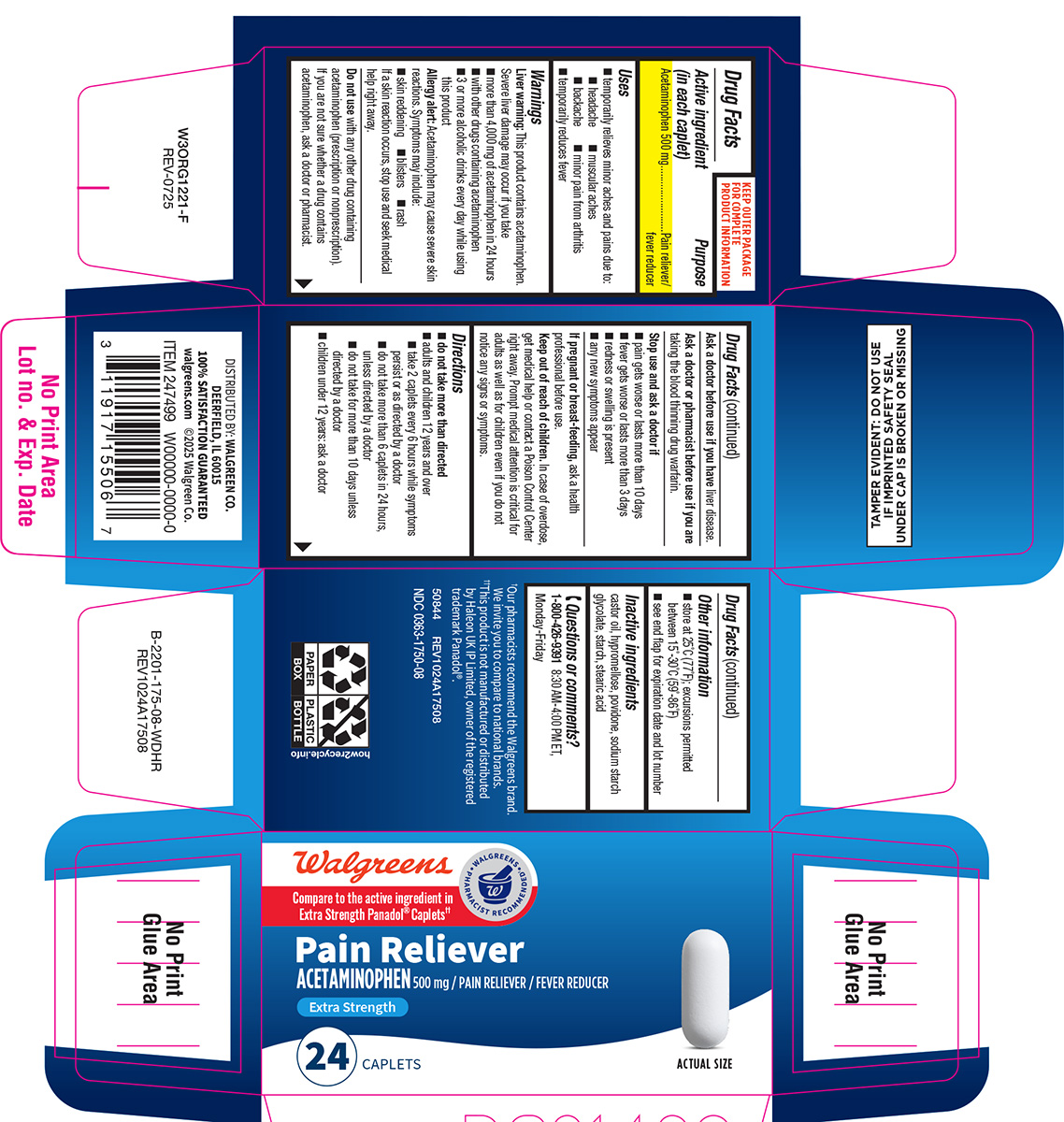 DRUG LABEL: Pain Reliever
NDC: 0363-1750 | Form: TABLET, FILM COATED
Manufacturer: Walgreen Company
Category: otc | Type: HUMAN OTC DRUG LABEL
Date: 20251211

ACTIVE INGREDIENTS: ACETAMINOPHEN 500 mg/1 1
INACTIVE INGREDIENTS: CASTOR OIL; HYPROMELLOSE, UNSPECIFIED; POVIDONE, UNSPECIFIED; SODIUM STARCH GLYCOLATE TYPE A POTATO; STARCH, CORN; STEARIC ACID

Pain Reliever

Active ingredient (in each caplet)

Acetaminophen 500 mg

Purpose

Pain reliever/fever reducer

Uses

- temporarily relieves minor aches and pains due to:
  - headache
  - muscular aches
  - backache
  - minor pain of arthritis

- temporarily reduces fever

Warnings

Liver warning: This product contains acetaminophen. Severe liver damage may occur if you take

- more than 4,000 mg of acetaminophen in 24 hours
- with other drugs containing acetaminophen
- 3 or more alcoholic drinks every day while using this product

Allergy alert: Acetaminophen may cause severe skin reactions. Symptoms may include:

- skin reddening
- blisters
- rash

If a skin reaction occurs, stop use and seek medical help right away.

Do not use

with any other drug containing acetaminophen (prescription or nonprescription). If you are not sure whether a drug contains acetaminophen, ask a doctor or pharmacist.

Ask a doctor before use if you have

liver disease.

Ask a doctor or pharmacist before use if you are

taking the blood thinning drug warfarin.

Stop use and ask a doctor if

- pain gets worse or lasts more than 10 days
- fever gets worse or lasts more than 3 days
- redness or swelling is present
- any new symptoms appear

If pregnant or breast-feeding,

ask a health professional before use.

Keep out of reach of children.

In case of overdose, get medical help or contact a Poison Control Center right away. Prompt medical attention is critical for adults as well as for children even if you do not notice any signs or symptoms.

Directions

- do not take more than directed
- adults and children 12 years and over
  - take 2 caplets every 6 hours while symptoms persist or as directed by a doctor
  - do not take more than 6 caplets in 24 hours, unless directed by a doctor
  - do not take for more than 10 days unless directed by a doctor
- children under 12 years: ask a doctor

Other information

- store at 25ºC (77ºF); excursions permitted between 15°-30°C (59°-86°F)
- see end flap for expiration date and lot number

Inactive ingredients

castor oil, hypromellose, povidone, sodium starch glycolate, starch, stearic acid

Questions or comments?

1-800-426-9391

Principal Display Panel

Walgreens
Compare to the active ingredient in
Panadol® Extra Strength Caplets††

• WALGREENS •
PHARMACIST RECOMMENDED†

NDC 0363-1750-08

Pain Reliever
ACETAMINOPHEN 500 mg / PAIN RELIEVER / FEVER REDUCER

EXTRA STRENGTH

24 CAPLETS

ACTUAL SIZE

TAMPER EVIDENT: DO NOT USE IF IMPRINTED
SAFETY SEAL UNDER CAP IS BROKEN OR MISSING

†Our pharmacists recommend the Walgreens brand.
We invite you to compare to national brands.

††This product is not manufactured or distributed
by Haleon UK IP Limited, owner of the registered
trademark Panadol®.

50844 REV1024A17508

DISTRIBUTED BY: WALGREEN CO.
DEERFIELD, IL 60015
100% SATISFACTION GUARANTEED
walgreens.com ©2025 Walgreen Co.

Walgreens 44-175